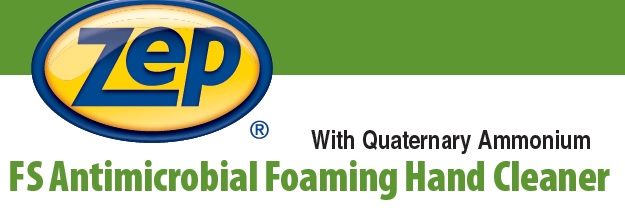 DRUG LABEL: Zep Fuzion FS Antimicrobial Foaming Hand Cleaner
NDC: 66949-132 | Form: LIQUID
Manufacturer: Zep Inc.
Category: otc | Type: HUMAN OTC DRUG LABEL
Date: 20251226

ACTIVE INGREDIENTS: BENZALKONIUM CHLORIDE 0.13 g/100 mL
INACTIVE INGREDIENTS: HEXANEDIOL; WATER; COCAMIDOPROPYL HYDROXYSULTAINE; LAURAMINE OXIDE; PEG-6 COCAMIDE; DIDECYLDIMONIUM CHLORIDE; PHENOXYETHANOL; IODOPROPYNYL BUTYLCARBAMATE; METHYLISOTHIAZOLINONE

66949-132 / 0996 Fuzion FS Antimicrobial Foaming

Active ingredient

Benzalkonium Chloride 0.13%

Purpose

Antiseptic Hand Wash

Uses

- Hand washing to decrease bacteria on the skin.
- For use in food processing facilities.

Warnings

For external use only.

Do not use in the eyes; if in eyes, rinse promptly and thoroughly with water.

Stop use and ask doctor if skin irritation or redness persists for more than 72 hours.

When using this product

- Do not swallow.
- If swallowed, do not induce vomiting and if individual is conscious, give large quantities of water to drink and consult a physician immediately.

Keep out of reach of children and pets. Children must be supervised in use of this product.

Directions

- Wet hands with water.
- Place hands under dispenser and apply liquid soap.
- Massage soap into hands and writsts, emphasizing back of hands, knuckles and cuticles.
- Rise hands thoroughly and dry.

Other information

- Store at 20 to 25°C (68 to 77°F).
- Do not freeze.
- Dispose in accordance with all applicable federal, state and local regulations.

Inactive ingredients

Water, Cocamidopropyl Hydroxysultaine, Lauramine Oxide, Didecyldimonium Chloride, PEG-6 Cocamide, Phenoxyethanol, Iodopropynyl Butylcarbamate, Methylisothiazolinone, Hexanediol

Questions or comments?

Call 1-800-I-BUY-ZEP (1-800-428-9937)